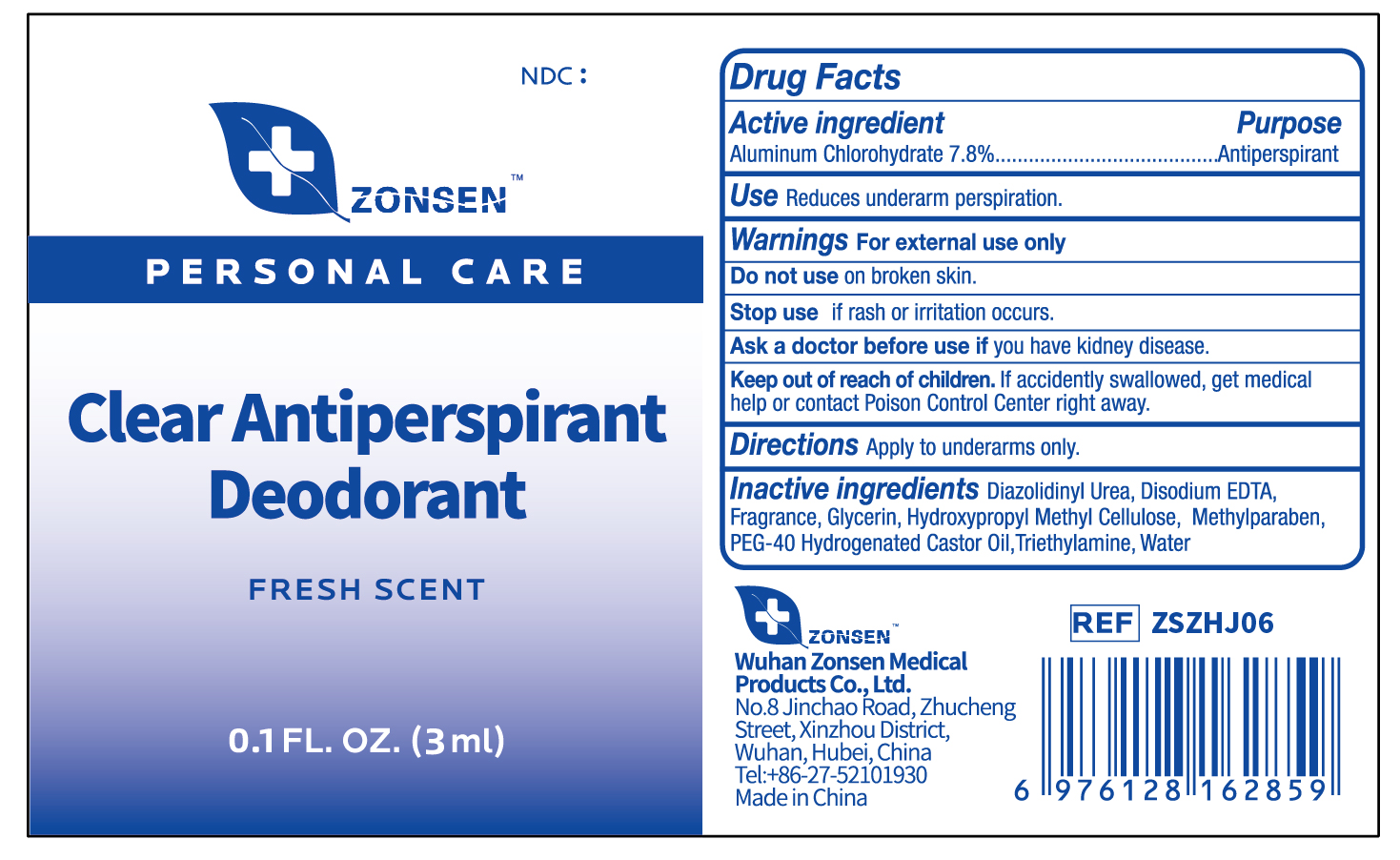 DRUG LABEL: ZONSEN Clear Antiperspirant Deodorant
NDC: 72932-017 | Form: LOTION
Manufacturer: Wuhan Zonsen Medical Products Co., Ltd.
Category: otc | Type: HUMAN OTC DRUG LABEL
Date: 20250603

ACTIVE INGREDIENTS: ALUMINUM CHLOROHYDRATE 78 mg/1 mL
INACTIVE INGREDIENTS: METHYLPARABEN; POLYOXYL 40 HYDROGENATED CASTOR OIL; GLYCERIN; DIAZOLIDINYL UREA; HYDROXYPROPYL METHYLCELLULOSE; EDETATE DISODIUM; WATER; TRIETHYLAMINE

Purpose

Antiperspirant

Active Ingredient

Aluminum Chlorohydrate 7.8%

Do not use

on broken skin.

Stop use

if rash or irritation occurs.

Ask a doctor before use

if you have kidney disease.

Keep out of reach of children

If accidently swallowed, get medical help or contact Poison Control Center right away.

Inactive Ingredient

Diazolidinyl Urea, Disodium EDTA, Fragrance, Glycerin, Hydroxyproply MethylCellulose, Methylparaben, PEG-40 Hydrogenated Castor Oil, Triethylamine, Water

Warnings

For external use only.

Directions

Apply to underarms only.

Use

Reduces underarm perspiration.

Dosage

Use daily for best results.

Label

ZONSEN

PERSONAL CARE

Clear Antiperspirant Deodorant

FRESH SCENT

0.1 FL. OZ.(3ml)